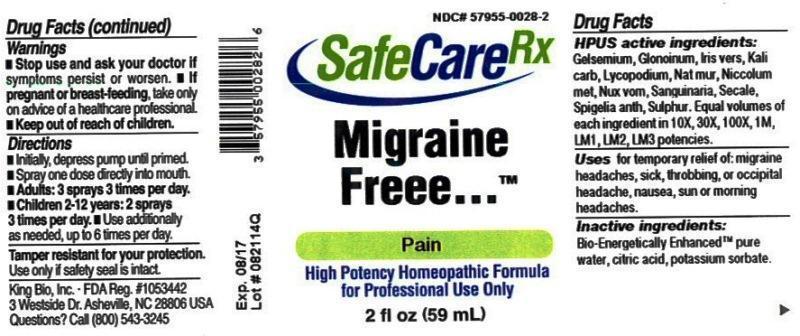 DRUG LABEL: Migraine Freee
NDC: 57955-0028 | Form: LIQUID
Manufacturer: King Bio Inc.
Category: homeopathic | Type: HUMAN OTC DRUG LABEL
Date: 20150218

ACTIVE INGREDIENTS: GELSEMIUM SEMPERVIRENS ROOT 10 [hp_X]/59 mL; NITROGLYCERIN 10 [hp_X]/59 mL; IRIS VERSICOLOR ROOT 10 [hp_X]/59 mL; POTASSIUM CARBONATE 10 [hp_X]/59 mL; LYCOPODIUM CLAVATUM SPORE 10 [hp_X]/59 mL; SODIUM CHLORIDE 10 [hp_X]/59 mL; STRYCHNOS NUX-VOMICA SEED 10 [hp_X]/59 mL; SANGUINARIA CANADENSIS ROOT 10 [hp_X]/59 mL; CLAVICEPS PURPUREA SCLEROTIUM 10 [hp_X]/59 mL; SPIGELIA ANTHELMIA 10 [hp_X]/59 mL; SULFUR 10 [hp_X]/59 mL; NICKEL 10 [hp_X]/59 mL
INACTIVE INGREDIENTS: WATER; ANHYDROUS CITRIC ACID; POTASSIUM SORBATE

Migraine Freee™

ACTIVE INGREDIENT

Drug Facts__________________________________________________________________________________________________________

HPUS active ingredients:Gelsemium sempervirens, Glonoinum, Iris versicolor, Kali carbonicum, Lycopodium clavatum, Natrum muriaticum, Nux vomica, Sanguinaria canadensis, Secale cornutum, Spigelia anthelmia, Sulphur, niccolum metallicum. Equal volumes of each ingredient in 10X, 30X, 100X, 1M, LM1, LM2, LM3 potencies.

INDICATIONS AND USAGE

Uses for temporary relief of: migraine headaches, sick, throbbing, or occipital headache, nausea, sun or morning headaches.

Inactive Ingredients:

Bio-Energetically Enhanced™ pure water, citric acid and potassium sorbate.

Warnings

- Stop use and ask your doctor if symptoms persist or worsen.
- If pregnant or breast-feeding, take only on advice of a healthcare professional.

- Keep out of reach of children.

Directions

- Initially, depress pump until primed.
- Spray one dose directly into mouth.
- Adults: 3 sprays 3 times per day.
- Children 2-12 years: 2 sprays 3 times per day.
- Use additionally as needed, up to 6 times per day.

OTHER SAFETY INFORMATION

Tamper resistant for your protection. Use only if safety seal is intact. This product has not been clinically tested.

PURPOSE

Uses for temporary relief of:

- migraine headaches
- sick, throbbing, or occipital headache
- nausea, sun or morning headaches